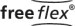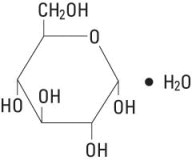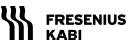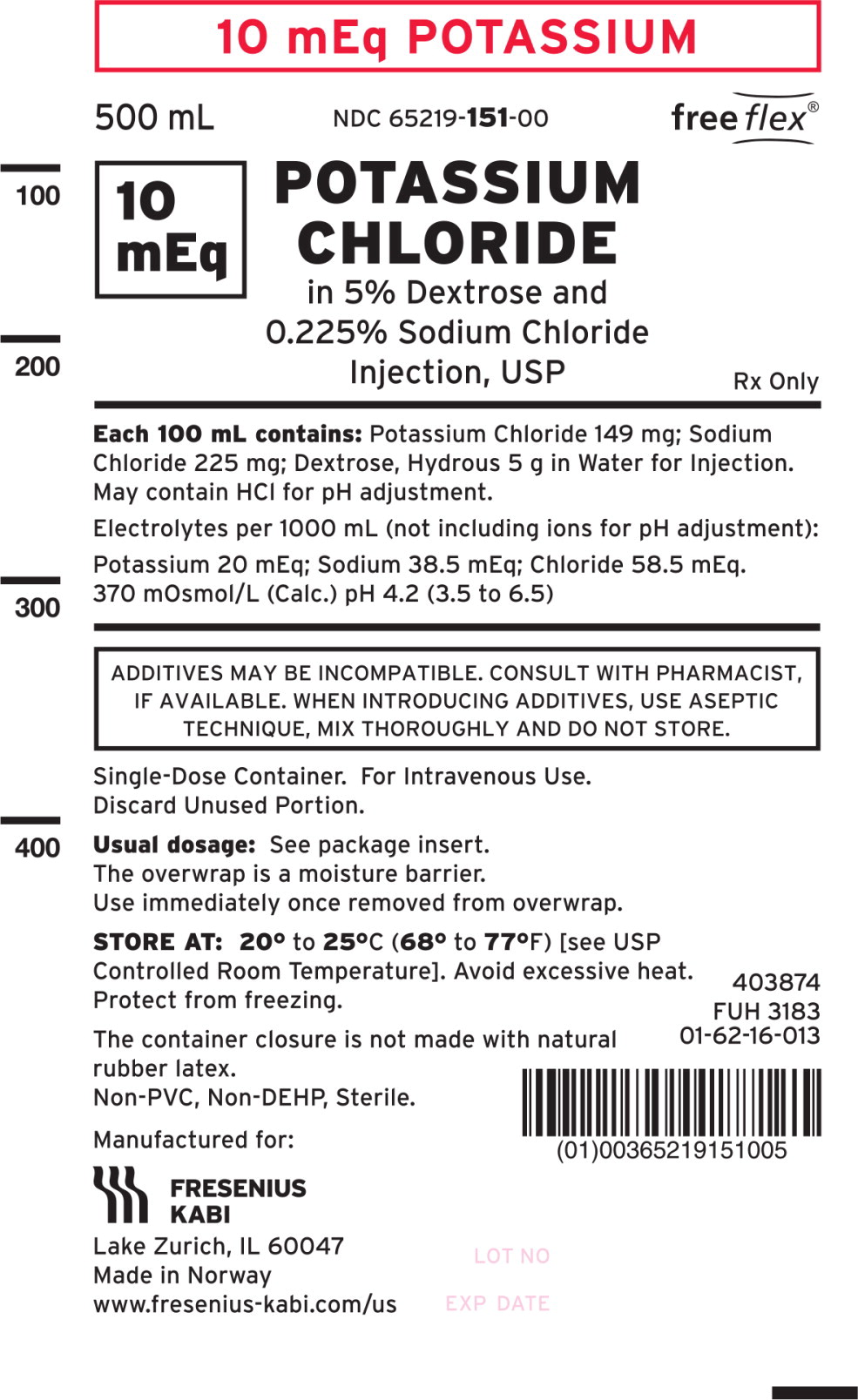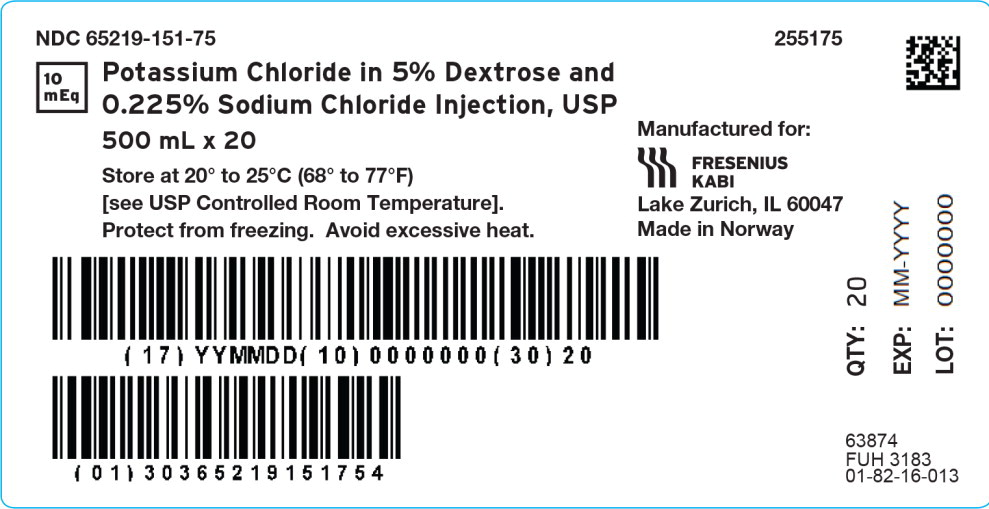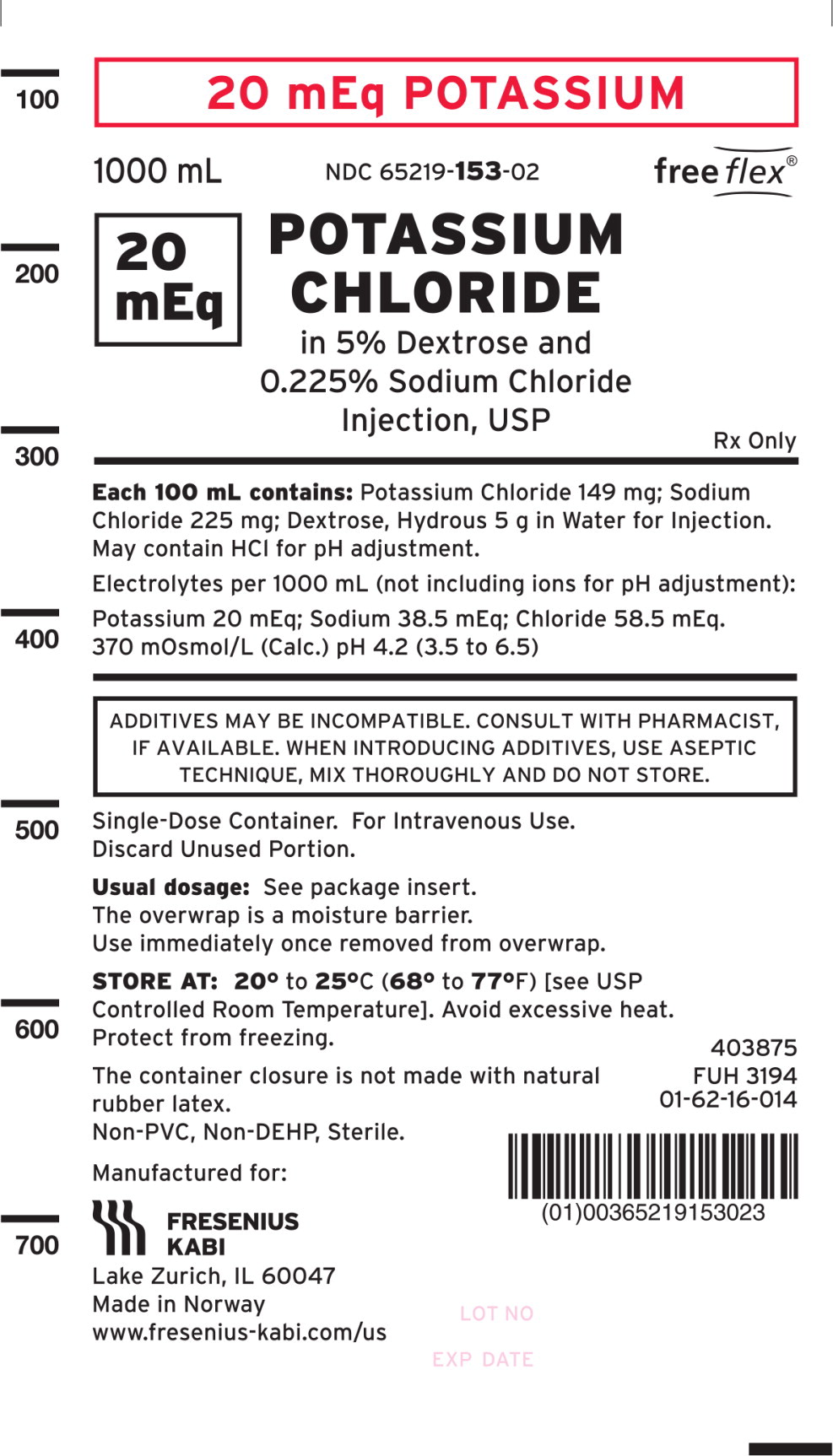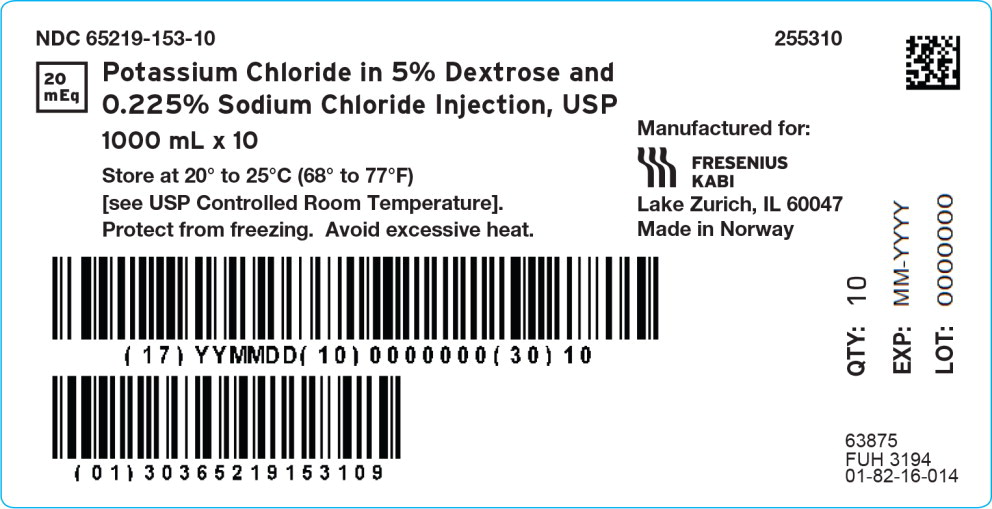 DRUG LABEL: Potassium Chloride in Dextrose and Sodium Chloride
NDC: 65219-151 | Form: INJECTION, SOLUTION
Manufacturer: Fresenius Kabi USA, LLC
Category: prescription | Type: HUMAN PRESCRIPTION DRUG LABEL
Date: 20240507

ACTIVE INGREDIENTS: DEXTROSE MONOHYDRATE 50 g/1000 mL; SODIUM CHLORIDE 2.25 g/1000 mL; POTASSIUM CHLORIDE 1.49 g/1000 mL
INACTIVE INGREDIENTS: WATER; HYDROCHLORIC ACID

POTASSIUM CHLORIDE IN DEXTROSE AND SODIUM CHLORIDE

Rx only

Potassium Chloride in 5% Dextrose and 0.225% Sodium Chloride Injection, USP

Flexible Plastic Container

DESCRIPTION

Intravenous solutions with potassium chloride (I.V. solutions with KCl) are sterile and nonpyrogenic solutions in water for injection. They are for administration by intravenous infusion only.

See table below for summary of content and characteristics of these solutions.

Table 1 |  | COMPOSITION (g/L) |  |  |  | Approx. Ionic Concentrations (mEq/L)
Potassium Chloride in 5% Dextrose and 0.225% Sodium Chloride Injection, USP |  | COMPOSITION (g/L) |  |  |  | Approx. Ionic Concentrations (mEq/L)
mEq Potassium | Size (mL) | Dextrose, Hydrous | Sodium Chloride | Potassium Chloride | Calculated Osmolarity (mOsmol/L) | pH | Sodium (Na^+) | Potassium (K^+) | Chloride (Cl^-) | Approximate Kcal/L
10 mEq | 500 | 50 | 2.25 | 1.49 | 370 | 4.2 (3.5 to 6.5) | 38.5 | 20 | 58.5 | 170
20 mEq | 1000 | 50 | 2.25 | 1.49 | 370 | 4.2 (3.5 to 6.5) | 38.5 | 20 | 58.5 | 170

May contain HCl for pH adjustment.

The solutions contain no bacteriostat, antimicrobial agent or added buffer and each is intended only for use as a single-dose injection. When smaller doses are required the unused portion should be discarded.

These solutions are parenteral fluid, nutrient and/or electrolyte replenishers.

Dextrose, USP is chemically designated D-glucose, monohydrate (C6H12O6 • H2O), a hexose sugar freely soluble in water. It has the following structural formula:

Potassium Chloride, USP is chemically designated KCl, a white granular powder freely soluble in water.

Sodium Chloride, USP is chemically designated NaCl, a white crystalline powder freely soluble in water.

Water for Injection, USP is chemically designated H2O.

The flexible plastic container is fabricated from a specially formulated non-plasticized, film containing polypropylene and thermoplastic elastomers (freeflex® bag). Water can permeate from inside the container into the overwrap but not in amounts sufficient to affect the solution significantly. Solutions in contact with the plastic container may leach out certain chemical components from the plastic in very small amounts; however, biological testing was supportive of the safety of the plastic container materials. Exposure to temperatures above 25°C/77°F during transport and storage will lead to minor losses in the moisture content. Higher temperatures lead to greater losses. It is unlikely that these minor losses will lead to clinically significant changes within the expiration period.

CLINICAL PHARMACOLOGY

When administered intravenously, these solutions provide a source of water and potassium chloride with carbohydrate (dextrose) and sodium chloride. See HOW SUPPLIED section for specific concentrations of these various solutions.

Solutions containing carbohydrate in the form of dextrose restore blood glucose levels and provide calories. Carbohydrate in the form of dextrose may aid in minimizing liver glycogen depletion and exerts a protein-sparing action. Dextrose injected parenterally undergoes oxidation to carbon dioxide and water.

Intravenous solutions containing potassium chloride are particularly intended to provide needed potassium cation (K^+). Potassium is the chief cation of body cells (160 mEq/liter of intracellular water). It is found in low concentration in plasma and extracellular fluids (3.5 to 5.0 mEq/liter in a healthy adult). Potassium plays an important role in electrolyte balance. Normally about 80 to 90% of the potassium intake is excreted in the urine; the remainder in the stools and to a small extent, in the perspiration. The kidney does not conserve potassium well so that during fasting or in patients on a potassium-free diet, potassium loss from the body continues resulting in potassium depletion. A deficiency of either potassium or chloride will lead to a deficit of the other.

Sodium chloride in water dissociates to provide sodium (Na^+) and chloride (Cl^−) ions. Sodium (Na^+) is the principal cation of the extracellular fluid and plays a large part in the therapy of fluid and electrolyte disturbances. Chloride (Cl^−) has an integral role in buffering action when oxygen and carbon dioxide exchange occurs in the red blood cells. The distribution and excretion of sodium (Na^+) and chloride (Cl^−) are largely under the control of the kidney which maintains a balance between intake and output.

Water is an essential constituent of all body tissues and accounts for approximately 70% of total body weight. Average normal adult daily requirement ranges from two to three liters (1.0 to 1.5 liters each for insensible water loss by perspiration and urine production).

Water balance is maintained by various regulatory mechanisms. Water distribution depends primarily on the concentration of electrolytes in the body compartments and sodium (Na^+) plays a major role in maintaining physiologic equilibrium.

INDICATIONS AND USAGE

These solutions are indicated in patients requiring parenteral administration of potassium chloride with minimal carbohydrate calories and sodium chloride.

CONTRAINDICATIONS

Solutions containing potassium chloride are contraindicated in diseases where high potassium levels may be encountered.

WARNINGS

Solutions which contain potassium ions should be used with great care, if at all, in patients with hyperkalemia, severe renal failure and in conditions in which potassium retention is present.

To avoid potassium intoxication, do not infuse these solutions rapidly. In patients with severe renal insufficiency or adrenal insufficiency, administration of potassium chloride may cause potassium intoxication.

Solutions containing sodium ions should be used with great care, if at all, in patients with congestive heart failure, severe renal insufficiency and in clinical states in which there exists edema with sodium retention.

In patients with diminished renal function, administration of solutions containing sodium or potassium ions may result in sodium or potassium retention.

The intravenous administration of these solutions can cause fluid and/or solute overloading resulting in dilution of serum electrolyte concentrations, overhydration, congested states or pulmonary edema.

The risk of dilutional states is inversely proportional to the electrolyte concentration of administered parenteral solutions. The risk of solute overload causing congested states with peripheral and pulmonary edema is directly proportional to the electrolyte concentrations of such solutions.

PRECAUTIONS

Clinical evaluation and periodic laboratory determinations are necessary to monitor changes in fluid balance, electrolyte concentrations and acid-base balance during prolonged parenteral therapy or whenever the condition of the patient warrants such evaluation.

Solutions containing dextrose should be used with caution in patients with known subclinical or overt diabetes mellitus.

Caution must be exercised in the administration of parenteral fluids, especially those containing sodium ions, to patients receiving corticosteroids or corticotropin.

Potassium replacement therapy should be guided primarily by serial electrocardiograms. Plasma potassium levels are not necessarily indicative of tissue potassium levels.

High plasma concentrations of potassium may cause death through cardiac depression, arrhythmias or arrest.

Potassium-containing solutions should be used with caution in the presence of cardiac disease, particularly in digitalized patients or in the presence of renal disease.

Care should be exercised to insure that the needle (or catheter) is well within the lumen of the vein and that extravasation does not occur.

Do not administer unless solution is clear and container is undamaged. Discard unused portion.

Carcinogenesis, Mutagenesis, Impairment of Fertility:

Studies with solutions from flexible plastic containers have not been performed to evaluate carcinogenic potential, mutagenic potential or effects on fertility.

PREGNANCY

Pregnancy Animal reproduction studies have not been conducted with dextrose, potassium chloride or sodium chloride. It is also not known whether dextrose, potassium chloride or sodium chloride can cause fetal harm when administered to a pregnant woman or can affect reproduction capacity. Dextrose, potassium chloride or sodium chloride should be given to a pregnant woman only if clearly needed.

Nursing Mothers:

Caution should be exercised when solutions from flexible plastic containers are administered to a nursing mother.

Pediatric Use:

The safety and effectiveness in the pediatric population are based on the similarity of the clinical conditions of the pediatric and adult populations. In neonates or very small infants the volume of fluid may affect fluid and electrolyte balance.

Frequent monitoring of serum glucose concentrations is required when dextrose is prescribed to pediatric patients, particularly neonates and low birth weight infants.

In very low birth weight infants, excessive or rapid administration of dextrose injection may result in increased serum osmolality and possible intracerebral hemorrhage.

Geriatric Use:

An evaluation of current literature revealed no clinical experience identifying differences in response between elderly and younger patients. In general, dose selection for an elderly patient should be cautious, usually starting at the low end of the dosing range, reflecting the greater frequency of decreased hepatic, renal, or cardiac function, and of concomitant disease or other drug therapy. Sodium and potassium ions are known to be substantially excreted by the kidney, and the risk of toxic reactions may be greater in patients with impaired renal function. Because elderly patients are more likely to have decreased renal function, care should be taken in dose selection, and it may be useful to monitor renal function.

ADVERSE REACTIONS

Reactions which may occur because of the solutions or technique of administration include febrile response, infection at the site of injection, venous thrombosis or phlebitis extending from the site of injection, extravasation and hypervolemia.

If an adverse reaction does occur, discontinue the infusion, evaluate the patient, institute appropriate therapeutic countermeasures and save the remainder of the fluid for examination if deemed necessary.

Nausea, vomiting, abdominal pain and diarrhea have been reported with potassium therapy. The signs and symptoms of potassium intoxication include paresthesias of the extremities, flaccid paralysis, listlessness, mental confusion, weakness and heaviness of the legs, hypotension, cardiac arrhythmias, heart block, electrocardiographic abnormalities such as disappearance of P waves, spreading and slurring of the QRS complex with development of a biphasic curve and cardiac arrest.

Potassium-containing solutions are intrinsically irritating to tissues. Therefore, extreme care should be taken to avoid perivascular infiltration. Local tissue necrosis and subsequent sloughing may result if extravasation occurs. Chemical phlebitis and venospasm have also been reported.

Should perivascular infiltration occur, I.V. administration at that site should be discontinued at once. Local infiltration of the affected area with procaine hydrochloride, 1%, to which hyaluronidase may be added, will often reduce venospasm and dilute the potassium remaining in the tissues locally. Local application of heat may also be helpful.

To report SUSPECTED ADVERSE REACTIONS, contact Fresenius Kabi USA, LLC at 1-800-551-7176 or FDA at 1-800-FDA-1088 or www.fda.gov/medwatch.

OVERDOSAGE

In the event of potassium overdosage, discontinue the infusion immediately and institute intensive corrective therapy to reduce serum potassium levels. See WARNINGS and PRECAUTIONS.

DOSAGE AND ADMINISTRATION

These solutions should be administered only by intravenous infusion and as directed by the physician. The dose and rate of injection are dependent upon the age, weight and clinical condition of the patient. If the serum potassium level is greater than 2.5 mEq/liter, potassium should be given at a rate not to exceed 10 mEq/hour in a concentration less than 30 mEq/liter. Somewhat faster rates and greater concentrations (usually up to 40 mEq/liter) of potassium may be indicated in patients with more severe potassium deficiency. The total 24- hour dose should not generally exceed 200 mEq of potassium.

As reported in the literature, the dosage and constant infusion rate of intravenous dextrose must be selected with caution in pediatric patients, particularly neonates and low birth weight infants, because of the increased risk of hyperglycemia/hypoglycemia.

Drug Interactions

Additives may be incompatible. Consult with pharmacist, if available. When introducing additives, use aseptic technique, mix thoroughly and do not store.

Parenteral drug products should be inspected visually for particulate matter and discoloration prior to administration, whenever solution and container permit. See PRECAUTIONS.

HOW SUPPLIED

Potassium Chloride in 5% Dextrose and 0.225% Sodium Chloride Injection, USP is supplied in single-dose freeflex® plastic containers as follows:

Product Code | Unit of Use | Strength | Unit of Sale
255175 | NDC 65219-151-00 One 500 mL freeflex® bag | 10 mEq Potassium Chloride | NDC 65219-151-75 Package of 20 freeflex® bags
255310 | NDC 65219-153-02 One 1000 mL freeflex® bag | 20 mEq Potassium Chloride | NDC 65219-153-10 Package of 10 freeflex® bags

Avoid excessive heat. Store at 20 to 25°C (68 to 77°F). [See USP Controlled Room Temperature.] Protect from freezing.

The container closure is not made with natural rubber latex. Non-PVC, Non-DEHP, Sterile.

INSTRUCTIONS FOR USE

Check flexible container solution composition, lot number, and expiry date.

Do not remove solution container from its overwrap until immediately before use. Use sterile equipment and aseptic technique.

Flexible Plastic Container (freeflex® bag)

To Open

1. Turn solution container over so that the text is face down. Using the pre-cut corner tabs, peel open the overwrap and remove solution container.
2. Check the solution container for leaks by squeezing firmly. If leaks are found, or if the seal is not intact, discard the solution.
3. Do not use if the solution is cloudy or a precipitate is present.

To Add Medication

1. Identify WHITE Additive Port with arrow pointing toward container.
2. Immediately before injecting additives, break off WHITE Additive Port Cap with the arrow pointing toward container.
3. Hold base of WHITE Additive Port horizontally.
4. Insert needle horizontally through the center of WHITE Additive Port's septum and inject additives.
5. Mix container contents thoroughly.

Preparation for Administration

1. Immediately before inserting the infusion set, break off BLUE Infusion Port Cap with the arrow pointing away from container.
2. Use a non-vented infusion set or close the air-inlet on a vented set.
3. Close the roller clamp of the infusion set.
4. Hold the base of BLUE Infusion Port.
5. Insert spike through BLUE Infusion Port by rotating wrist slightly until the spike is inserted. NOTE: See full directions accompanying administration set.

WARNING: Do not use flexible container in series connections.

Manufactured for:

Lake Zurich, Illinois 60047

Made in Norway

451749
www.fresenius-kabi.com/us

Issued: May 2022

PACKAGE LABEL - PRINCIPAL DISPLAY – Potassium Chloride in 5% Dextrose and 0.225% Sodium Chloride Injection, USP Bag Label

10 mEq POTASSIUM

500 mL NDC 65219-151-00 freeflex®
10 mEq POTASSIUM CHLORIDE

in 5% Dextrose and 0.225% Sodium Chloride Injection, USP

Rx Only

PACKAGE LABEL - PRINCIPAL DISPLAY – Potassium Chloride in 5% Dextrose and 0.225% Sodium Chloride Injection, USP Case Label

NDC 65219-151-75

10 mEq Potassium Chloride in 5% Dextrose and 0.225% Sodium Chloride Injection, USP

500 mL x 20

Store at 20° to 25°C (68° to 77°F)

[see USP Controlled Room Temperature].

Protect from freezing. Avoid excessive heat.

PACKAGE LABEL - PRINCIPAL DISPLAY – Potassium Chloride in 5% Dextrose and 0.225% Sodium Chloride Injection, USP Bag Label

20 mEq POTASSIUM

1000 mL NDC 65219-153-02 freeflex®
20 mEq POTASSIUM CHLORIDE

in 5% Dextrose and 0.225% Sodium Chloride Injection, USP

Rx Only

PACKAGE LABEL - PRINCIPAL DISPLAY – Potassium Chloride in 5% Dextrose and 0.225% Sodium Chloride Injection, USP Case Label

NDC 65219-153-10

20 mEq Potassium Chloride in 5% Dextrose and 0.225% Sodium Chloride Injection, USP

1000 mL x 10

Store at 20° to 25°C (68° to 77°F)

[see USP Controlled Room Temperature].

Protect from freezing. Avoid excessive heat.